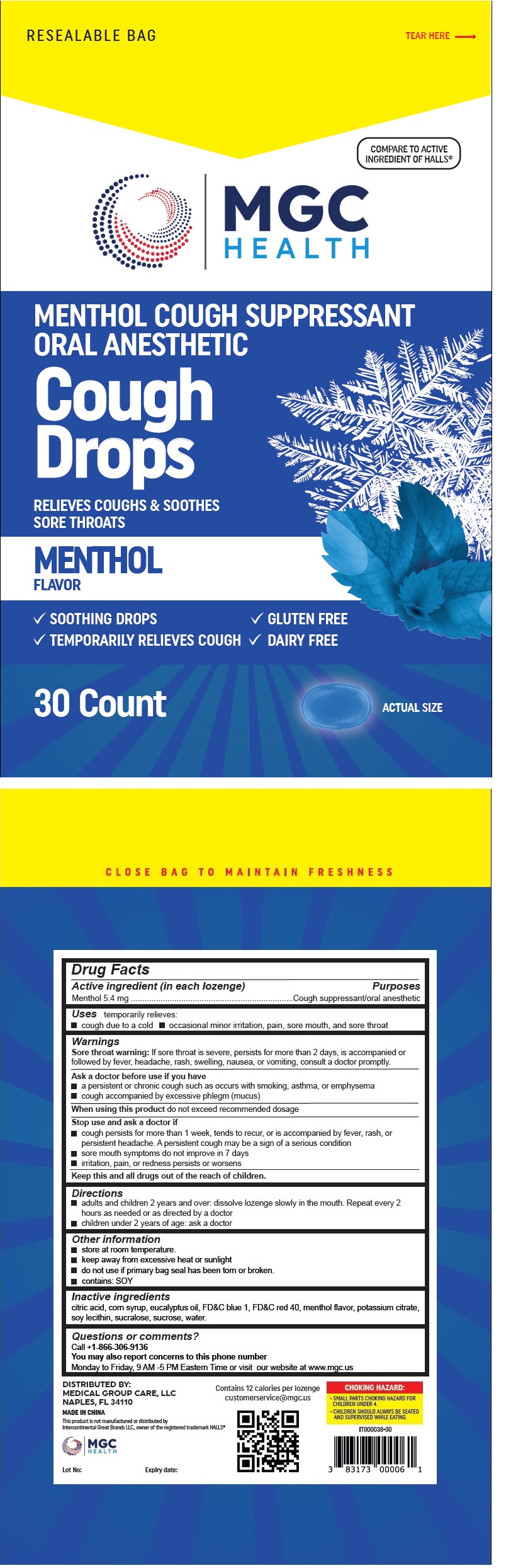 DRUG LABEL: MENTHOL COUGH SUPPRESSANT ORAL ANESTHETIC Cough Drops
NDC: 83698-110 | Form: LOZENGE
Manufacturer: Xiamen Kang Zhongyuan Biotechnology Co., Ltd.
Category: otc | Type: HUMAN OTC DRUG LABEL
Date: 20251229

ACTIVE INGREDIENTS: MENTHOL, UNSPECIFIED FORM 5.4 mg/1 1
INACTIVE INGREDIENTS: CITRIC ACID MONOHYDRATE; CORN SYRUP; EUCALYPTUS OIL; FD&C BLUE NO. 1; FD&C RED NO. 40; POTASSIUM CITRATE; SOYBEAN LECITHIN; SUCRALOSE; SUCROSE; WATER

MENTHOL COUGH SUPPRESSANT ORAL ANESTHETIC Cough Drops

Active ingredient (in each lozenge)

Menthol 5.4 mg

Purposes

Cough suppressant/oral anesthetic

Uses

temporarily relieves:
• cough due to a cold • occasional minor irritation, pain, sore mouth, and sore throat

Warnings

Sore throat warning:If sore throat is severe, persists for more than 2 days, is accompanied or followed by fever, headache, rash, swelling, nausea, or vomiting, consult a doctor promptly.

Ask a doctor before use if you have
• a persistent or chronic cough such as occurs with smoking, asthma, or emphysema
• cough accompanied by excessive phlegm (mucus)

When using this productdo not exceed recommended dosage

Stop use and ask a doctor if
• cough persists for more than 1 week, tends to recur, or is accompanied by fever, rash, or persistent headache. A persistent cough may be a sign of a serious condition
• sore mouth symptoms do not improve in 7 days
• irritation, pain, or redness persists or worsens

KEEP OUT OF REACH OF CHILDREN

Keep this and all drugs out of the reach of children.

Directions

• adults and children 2 years and over: dissolve lozenge slowly in the mouth. Repeat every 2 hours as needed or as directed by a doctor
• children under 2 years of age: ask a doctor

Other information

• store at room temperature.
• keep away from excessive heat or sunlight
• do not use if primary bag seal has been torn or broken.
• contains: SOY

Inactive ingredients

citric acid, corn syrup, eucalyptus oil, FD&C blue 1, FD&C red 40, menthol flavor, potassium citrate, soy lecithin, sucralose, sucrose, water.

Questions or comments?

Call +1-866-306-9136
You may also report concerns to this phone number
Monday to Friday, 9 AM -5 PM Eastern Time or visit our website at www.mgc.us

RESEALABLE BAG

COMPARE TO ACTIVE INGREDIENT OF HALLS®

MENTHOL FLAVOR

√ SOOTHING DROPS
√ GLUTEN FREE
√ DAIRY FREE

CLOSE BAG TO MAINTAIN FRESHNESS

DISTRIBUTED BY:
MEDICAL GROUP CARE, LLC
NAPLES, FL 34110

MADE IN CHINA

This product is not manufactured or distributed by
Intercontinental Great Brands LLC., owner of the registered trademark HALLS®

Contains 12 calories per lozenge
customerservice@mgc.us

CHOKING HAZARD:
• SMALL PARTS CHOKING HAZARD FOR CHILDREN UNDER 4.
• CHILDREN SHOULD ALWAYS BE SEATED AND SUPERVISED WHILE EATING.